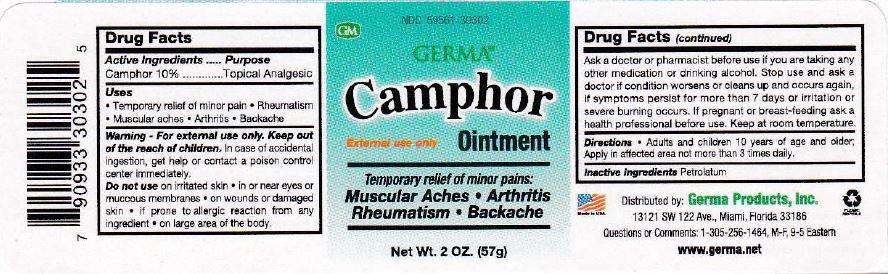 DRUG LABEL: Camphor
NDC: 59561-703 | Form: OINTMENT
Manufacturer: Caribe Natural, Inc
Category: otc | Type: HUMAN OTC DRUG LABEL
Date: 20150505

ACTIVE INGREDIENTS: CAMPHOR (NATURAL) 10 g/100 g
INACTIVE INGREDIENTS: PETROLATUM; ALCOHOL; CYCLOMETHICONE

Active Ingredients ............. Purpose

Camphor 10% ............. Topical Analgesic

Uses

- Temporary relief of minor pain
- Rheumatism
- Muscular Aches
- Arthritis
- Backache

Keep out of the reach of children.

INDICATIONS AND USAGE

Camphor Ointment

External Use Only

Temporary relief of minor pains:

Muscular Aches | Arthritis

Rheumatism | Backache

DOSAGE AND ADMINISTRATION

Directions - Adults and children 10 years of age and older: apply in affected area not more than 3 times daily.

WARNINGS

Warning - For external use only.

In case of accidental ingestion, get help or contact a poison control center immediately.

Do not use

- on irritated skin
- in or near eyes or mucous membranes
- on wounds or damaged skin
- if prone to allergic reaction from any ingredient
- on large area of the body

Ask a doctor or pharmacist before use if you are taking any other medication or drinking alcohol. Stop use and ask a doctor if condition worsens or clears up and occurs again, if symptoms persist for more than 7 days or irritation or severe burning occurs. If pregnant or breast-feeding ask a health professional before use. Keep at room temperature.

Inactive Ingredients Petrolatum